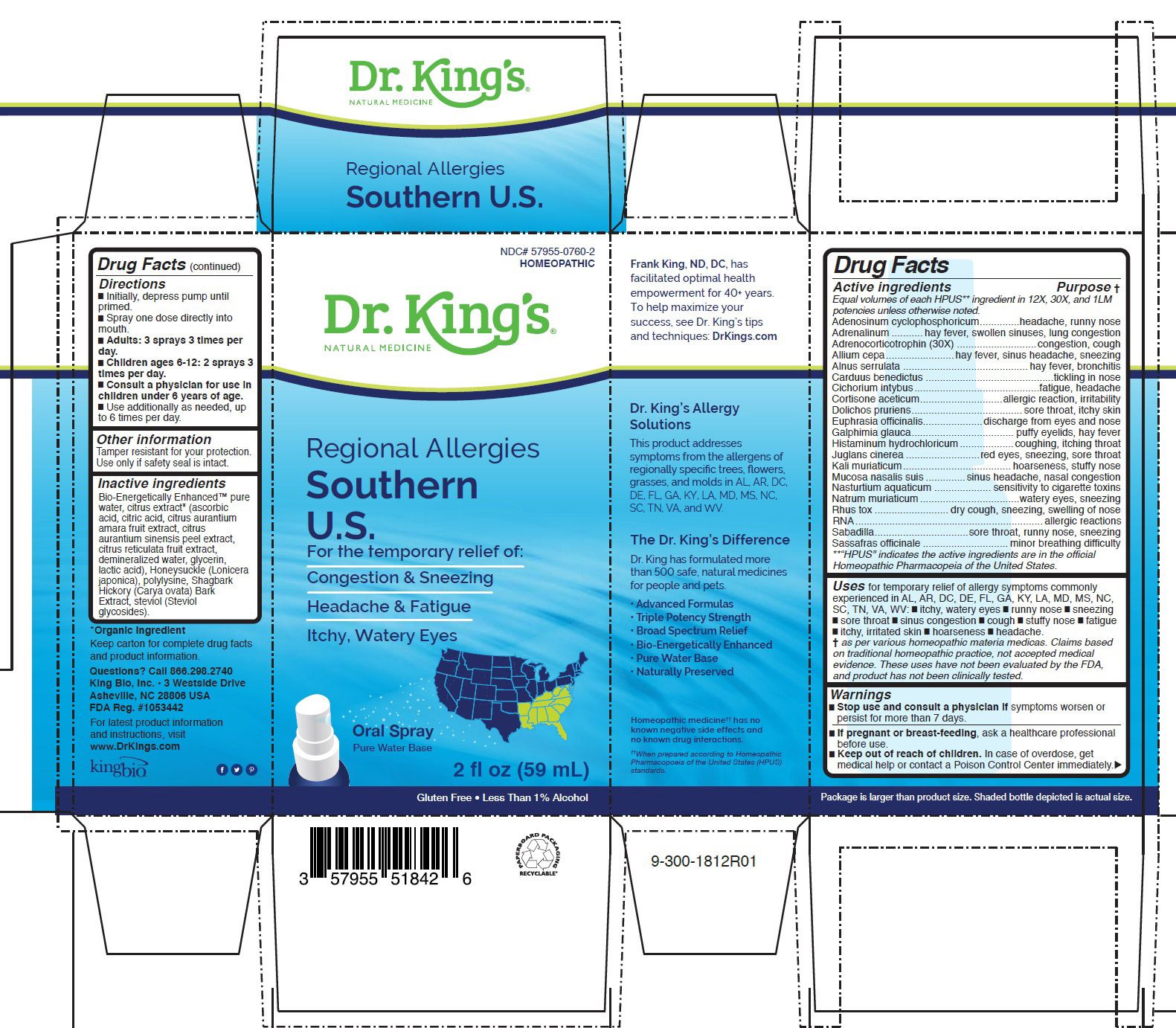 DRUG LABEL: Regional Allergies Southern U.S.
NDC: 57955-0760 | Form: LIQUID
Manufacturer: King Bio Inc.
Category: homeopathic | Type: HUMAN OTC DRUG LABEL
Date: 20200709

ACTIVE INGREDIENTS: ADENOSINE CYCLIC PHOSPHATE 12 [hp_X]/59 mL; EPINEPHRINE 12 [hp_X]/59 mL; CORTICOTROPIN 30 [hp_X]/59 mL; ONION 12 [hp_X]/59 mL; ALNUS SERRULATA BARK 12 [hp_X]/59 mL; CENTAUREA BENEDICTA 12 [hp_X]/59 mL; CHICORY ROOT 12 [hp_X]/59 mL; CORTISONE ACETATE 12 [hp_X]/59 mL; MUCUNA PRURIENS FRUIT TRICHOME 12 [hp_X]/59 mL; EUPHRASIA STRICTA 12 [hp_X]/59 mL; GALPHIMIA GLAUCA FLOWERING TOP 12 [hp_X]/59 mL; HISTAMINE DIHYDROCHLORIDE 12 [hp_X]/59 mL; JUGLANS CINEREA BRANCH BARK/ROOT BARK 12 [hp_X]/59 mL; POTASSIUM CHLORIDE 12 [hp_X]/59 mL; SUS SCROFA NASAL MUCOSA 12 [hp_X]/59 mL; NASTURTIUM OFFICINALE 12 [hp_X]/59 mL; SODIUM CHLORIDE 12 [hp_X]/59 mL; SACCHAROMYCES CEREVISIAE RNA 12 [hp_X]/59 mL; TOXICODENDRON PUBESCENS LEAF 12 [hp_X]/59 mL; SCHOENOCAULON OFFICINALE SEED 12 [hp_X]/59 mL; SASSAFRAS ALBIDUM ROOT BARK 12 [hp_X]/59 mL
INACTIVE INGREDIENTS: WATER; CARYA OVATA BARK; CITRUS BIOFLAVONOIDS; LONICERA JAPONICA FLOWER; POLYEPSILON-LYSINE (4000 MW); REBAUDIOSIDE A

Regional Allergies Southern U.S.

Drug Facts

____________________________________________________________________________________________________________

HPUS active ingredients: Adenosinum cyclophosphoricum, Adrenalinum, Adrenocorticotrophin (30X), Allium cepa, Alnus serrulata, Carduus benedictus, Cichorium intybus, Cortisone aceticum, Dolichos pruriens, Euphrasia officinalis, Galphimia glauca, Histaminum hydrochloricum,Juglans cinerea, Kali muriaticum, Mucosa nasalis suis, Nasturtium aquaticum, Natrum muriaticum, Rhus tox, RNA, Sabadilla, Sassafras officinale.

Equal volumes of each ingredient in 12X, 30X, and 1LM.

Uses

for temporary relief of allergy symptoms commonly
experienced in AL, AR, DC, DE, FL, GA, KY, LA, MD, MS, NC,
SC, TN, VA, WV: █ itchy, watery eyes █ runny nose █ sneezing
█ sore throat █ sinus congestion █ cough █ stuffy nose █ fatigue
█ itchy, irritated skin █ hoarseness █ headache.

Warnings

Stop use and consult a physician if symptoms worsen or
persist for more than 7 days.

PREGNANCY OR BREAST FEEDING

If pregnant or breast-feeding, ask a healthcare professional
before use.

Keep out of reach of children. In case of overdose, get
medical help or contact a Poison Control Center immediately.

Directions:

█ Initially, depress pump until
primed.
█ Spray one dose directly into
mouth.
█ Adults: 3 sprays 3 times per
day.
█ Children ages 6-12: 2 sprays 3
times per day.
█ Consult a physician for use in
children under 6 years of age.
█ Use additionally as needed, up
to 6 times per day

STORAGE AND HANDLING

Tamper resistant for your protection. Use only if safety seal is intact.

INACTIVE INGREDIENT

Bio-Energetically Enhanced™ pure
water, citrus extract* (ascorbic
acid, citric acid, citrus aurantium
amara fruit extract, citrus
aurantium sinensis peel extract,
citrus reticulata fruit extract,
demineralized water, glycerin,
lactic acid), Honeysuckle (Lonicera
japonica), polylysine, Shagbark
Hickory (Carya ovata) Bark
Extract, steviol (Steviol
glycosides).

HPUS active ingredients Purpose

Equal volumes of each HPUS** ingredient in 12X, 30X, and 1LM
potencies unless otherwise noted.
Adenosinum cyclophosphoricum..............headache, runny nose
Adrenalinum ...........hay fever, swollen sinuses, lung congestion
Adrenocorticotrophin (30X) ............................congestion, cough
Allium cepa........................hay fever, sinus headache, sneezing
Alnus serrulata ............................................hay fever, bronchitis
Carduus benedictus .............................................tickling in nose
Cichorium intybus............................................fatigue, headache
Cortisone aceticum.............................allergic reaction, irritability
Dolichos pruriens.......................................sore throat, itchy skin
Euphrasia officinalis.....................discharge from eyes and nose
Galphimia glauca.................................... puffy eyelids, hay fever
Histaminum hydrochloricum...................coughing, itching throat
Juglans cinerea ..........................red eyes, sneezing, sore throat
Kali muriaticum......................................hoarseness, stuffy nose
Mucosa nasalis suis ..............sinus headache, nasal congestion
Nasturtium aquaticum .................... sensitivity to cigarette toxins
Natrum muriaticum...................................watery eyes, sneezing
Rhus tox .......................... dry cough, sneezing, swelling of nose
RNA..................................................................allergic reactions
Sabadilla.................................sore throat, runny nose, sneezing
Sassafras officinale ..............................minor breathing difficulty
**“HPUS” indicates the active ingredients are in the official
Homeopathic Pharmacopeia of the United States.

Questions? Call 866.298.2740
King Bio, Inc. • 3 Westside Drive
Asheville, NC 28806 USA
FDA Reg. #1053442

For latest product information
and instructions, visit
www.DrKings.com